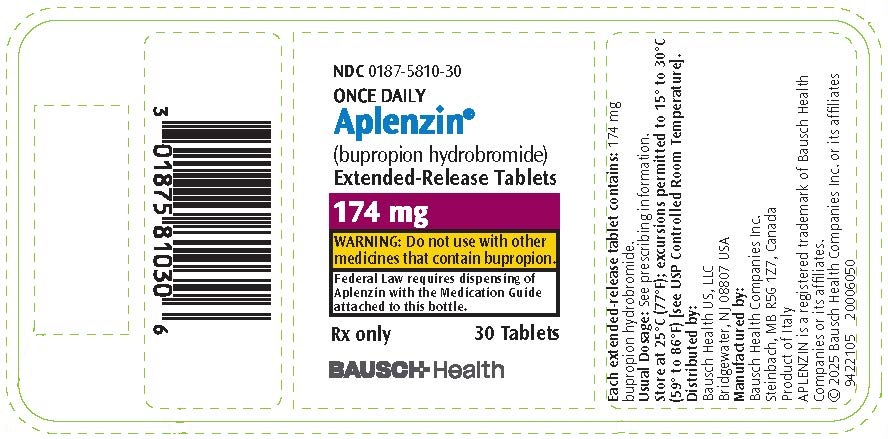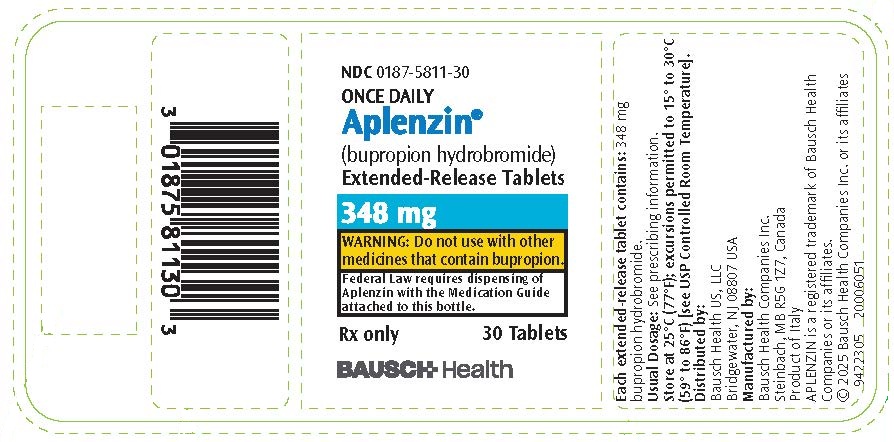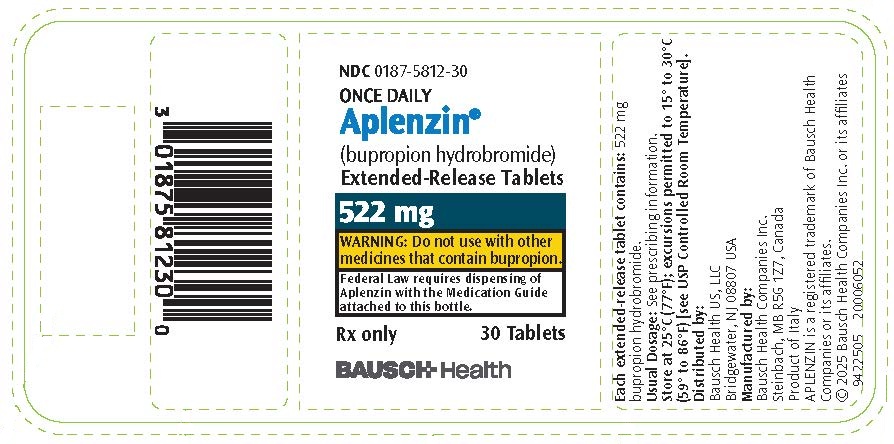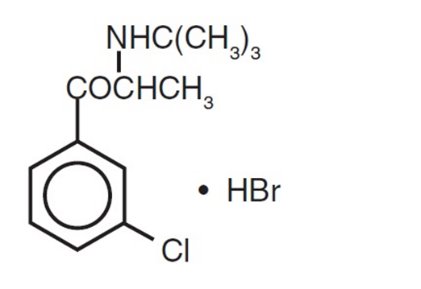 DRUG LABEL: Aplenzin
NDC: 0187-5810 | Form: TABLET, EXTENDED RELEASE
Manufacturer: Bausch Health US, LLC
Category: prescription | Type: HUMAN PRESCRIPTION DRUG LABEL
Date: 20260217

ACTIVE INGREDIENTS: BUPROPION HYDROBROMIDE 174 mg/1 1
INACTIVE INGREDIENTS: GLYCERYL DIBEHENATE; DIBUTYL SEBACATE; CARNAUBA WAX; ETHYLCELLULOSE, UNSPECIFIED; POLYVINYL ALCOHOL, UNSPECIFIED; POLYETHYLENE GLYCOL, UNSPECIFIED; CROSPOVIDONE, UNSPECIFIED

HIGHLIGHTS OF PRESCRIBING INFORMATION

These highlights do not include all the information needed to use APLENZIN safely and effectively. See full prescribing information for APLENZIN.
APLENZIN® (bupropion hydrobromide) extended-release tablets, for oral use
Initial U.S. Approval: 1985

WARNING: SUICIDAL THOUGHTS AND BEHAVIORS

See full prescribing information for complete boxed warning.

- Increased risk of suicidal thinking and behavior in children, adolescents, and young adults taking antidepressants. Monitor for worsening and emergence of suicidal thoughts and behaviors. (5.1)

1 INDICATIONS AND USAGE

APLENZIN is an aminoketone antidepressant, indicated for the treatment of major depressive disorder (MDD) and seasonal affective disorder (SAD). Periodically reevaluate long-term usefulness for the individual patient. (1)

2 DOSAGE AND ADMINISTRATION

General

- Increase dose gradually to reduce seizure risk. (2.1, 5.3)

Major Depressive Disorder

- Starting dose: 174 mg once daily (equivalent to 150 mg bupropion HCl). Usual target dose: 348 mg once daily (equivalent to 300 mg bupropion HCl). (2.3)
- After 4 days, may increase the dose to 348 mg once daily. (2.3)

Seasonal Affective Disorder

- Initiate treatment in the autumn prior to onset of seasonal depressive symptoms. (2.4)
- Starting dose: 174 mg once daily (equivalent to 150 mg bupropion HCl). Usual target dose: 348 mg once daily (equivalent to 300 mg bupropion HCl). (2.4)
- After one week, may increase the dose to 348 mg once daily. (2.4)
- Continue treatment through the winter season. (2.4)

Hepatic Impairment

- Moderate to severe hepatic impairment: Maximum dose 174 mg every other day (2.6)
- Mild hepatic impairment: Consider reducing the dose and/or frequency of dosing. (2.2, 2.6, 8.7)

Renal Impairment

- Consider reducing the dose and/or frequency of dosing. (2.2, 2.7, 8.6)

3 DOSAGE FORMS AND STRENGTHS

Extended-release tablets: 174 mg, 348 mg, 522 mg (3)

4 CONTRAINDICATIONS

- Seizure disorder. (4, 5.3)
- Current or prior diagnosis of bulimia or anorexia nervosa. (4, 5.3)
- Abrupt discontinuation of alcohol, benzodiazepines, barbiturates, antiepileptic drugs. (4, 5.3)
- Monoamine Oxidase Inhibitors (MAOIs): Do not use MAOIs intended to treat psychiatric disorders with APLENZIN or within 14 days of stopping an MAOI intended to treat psychiatric disorders. In addition, do not start APLENZIN in a patient who is being treated with linezolid or intravenous methylene blue. (4, 7.6)
- Known hypersensitivity to bupropion or other ingredients of APLENZIN. (4, 5.8)

5 WARNINGS AND PRECAUTIONS

- Neuropsychiatric Adverse Events During Smoking Cessation: Postmarketing reports of serious or clinically significant neuropsychiatric adverse events have included changes in mood (including depression and mania), psychosis, hallucinations, paranoia, delusions, homicidal ideation, aggression, hostility, agitation, anxiety, and panic, as well as suicidal ideation, suicide attempt, and completed suicide. Observe patients attempting to quit smoking with APLENZIN for the occurrence of such symptoms and instruct them to discontinue APLENZIN and contact a healthcare provider if they experience such adverse events. (5.2)
- Seizure Risk: The risk is dose-related. Can minimize risk by limiting daily dose to 522 mg and gradually increasing the dose. Discontinue if seizure occurs. (4, 5.3, 7.3)
- Hypertension: APLENZIN can increase blood pressure. Monitor blood pressure before initiating treatment and periodically during treatment. (5.4)
- Activation of Mania/Hypomania: Screen patients for bipolar disorder and monitor for these symptoms. (5.5)
- Psychosis and Other Neuropsychiatric Reactions: Instruct patients to contact a healthcare professional if such reactions occur. (5.6)
- Angle-Closure Glaucoma: Angle-closure glaucoma has occurred in patients with untreated anatomically narrow angles treated with antidepressants. (5.7)

6 ADVERSE REACTIONS

Most common adverse reactions are (incidence ≥5%; ≥2× placebo rate): dry mouth, nausea, insomnia, dizziness, pharyngitis, abdominal pain, agitation, anxiety, tremor, palpitation, sweating, tinnitus, myalgia, anorexia, urinary frequency, rash. (6.1)

To report SUSPECTED ADVERSE REACTIONS, contact Bausch Health US, LLC at 1-800-321-4576 or FDA at 1-800-FDA-1088 or www.fda.gov/medwatch.

7 DRUG INTERACTIONS

- CYP2B6 inducers: Dose increase may be necessary if coadministered with CYP2B6 inducers (e.g., ritonavir, lopinavir, efavirenz, carbamazepine, phenobarbital, phenytoin) based on clinical exposure, but should not exceed the maximum dose. (7.1)
- Drugs metabolized by CYP2D6: Bupropion inhibits CYP2D6 and can increase concentrations of: antidepressants (e.g., venlafaxine, nortriptyline, imipramine, desipramine, paroxetine, fluoxetine, sertraline), antipsychotics (e.g., haloperidol, risperidone, thioridazine), beta-blockers (e.g., metoprolol), and Type 1C antiarrhythmics (e.g., propafenone, flecainide). Consider dose reduction when using with bupropion. (7.2)
- Drugs that lower seizure threshold: Dose APLENZIN with caution. (5.3, 7.3)
- Dopaminergic Drugs (levodopa and amantadine): CNS toxicity can occur when used concomitantly with APLENZIN. (7.4)
- MAOIs: Increased risk of hypertensive reactions can occur when used concomitantly with APLENZIN. (7.6)
- Drug-laboratory test interactions: APLENZIN can cause false-positive urine test results for amphetamines. (7.7)

FULL PRESCRIBING INFORMATION

WARNING: SUICIDAL THOUGHTS AND BEHAVIORS

SUICIDALITY AND ANTIDEPRESSANT DRUGS

Antidepressants increased the risk of suicidal thoughts and behavior in children, adolescents, and young adults in short-term trials. These trials did not show an increase in the risk of suicidal thoughts and behavior with antidepressant use in subjects aged 65 and older [see Warnings and Precautions (5.1)].

In patients of all ages who are started on antidepressant therapy, monitor closely for worsening, and for emergence of suicidal thoughts and behaviors. Advise families and caregivers of the need for close observation and communication with the prescriber [see Warnings and Precautions (5.1)].

1 INDICATIONS AND USAGE

1.1 Major Depressive Disorder

APLENZIN® (bupropion hydrobromide) extended-release tablets are indicated for the treatment of major depressive disorder (MDD), as defined by the Diagnostic and Statistical Manual (DSM).

The efficacy of the immediate-release formulation of bupropion was established in two 4-week controlled inpatient trials and one 6-week controlled outpatient trial of adult patients with MDD. The efficacy of the sustained-release formulation of bupropion in the maintenance treatment of MDD was established in a long-term (up to 44 weeks), placebo-controlled trial in patients who had responded to bupropion in an 8-week study of acute treatment [see Clinical Studies (14.1)].

1.2 Seasonal Affective Disorder

APLENZIN is indicated for the prevention of seasonal major depressive episodes in patients with a diagnosis of seasonal affective disorder (SAD).

The efficacy of bupropion hydrochloride extended-release tablets in the prevention of seasonal major depressive episodes was established in 3 placebo-controlled trials in adult outpatients with a history of MDD with an autumn-winter seasonal pattern as defined in the DSM [see Clinical Studies (14.2)].

2 DOSAGE AND ADMINISTRATION

2.1 General Instructions for Use

To minimize the risk of seizure, increase the dose gradually [see Warnings and Precautions (5.3)].

APLENZIN should be swallowed whole and not crushed, divided, or chewed. APLENZIN should be administered in the morning and may be taken with or without regard to meals.

2.2 Equivalent Daily Doses of APLENZIN (Bupropion hydrobromide) and Bupropion hydrochloride

See Table 1 for equivalent daily doses of APLENZIN (bupropion hydrobromide) and bupropion hydrochloride.

Table 1: Equivalent Daily Doses of APLENZIN (Bupropion hydrobromide) and Bupropion hydrochloride
APLENZIN (Bupropion hydrobromide) | Bupropion hydrochloride
522 mg | 450 mg
348 mg | 300 mg
174 mg | 150 mg

2.3 Dosage for Major Depressive Disorder (MDD)

The recommended starting dose for MDD is 174 mg once daily in the morning. After 4 days of dosing, the dose may be increased to the target dose of 348 mg once daily in the morning.

It is generally agreed that acute episodes of depression require several months or longer of antidepressant treatment beyond the response in the acute episode. It is unknown whether the APLENZIN dose needed for maintenance treatment is identical to the dose that provided an initial response. Periodically reassess the need for maintenance treatment and the appropriate dose for such treatment.

2.4 Dosage for Seasonal Affective Disorder (SAD)

The recommended starting dose for SAD is 174 mg once daily. After 7 days of dosing, the dose may be increased to the target dose of 348 mg once daily in the morning. Doses above 300 mg of bupropion HCl extended-release (equivalent to APLENZIN 348 mg) were not assessed in the SAD trials.

For the prevention of seasonal MDD episodes associated with SAD, initiate APLENZIN in the autumn, prior to the onset of depressive symptoms. Continue treatment through the winter season. Taper and discontinue APLENZIN in early spring. For patients treated with 348 mg per day, decrease the dose to 174 mg once daily before discontinuing APLENZIN. Individualize the timing of initiation, and duration of treatment should be individualized, based on the patient’s historical pattern of seasonal MDD episodes.

2.5 To Discontinue APLENZIN, Taper the Dose

When discontinuing treatment in patients treated with APLENZIN 348 mg once daily, decrease the dose to 174 mg once daily prior to discontinuation.

2.6 Dosage Adjustment in Patients with Hepatic Impairment

In patients with moderate to severe hepatic impairment (Child-Pugh score: 7 to 15), the maximum dose is 174 mg every other day. In patients with mild hepatic impairment (Child-Pugh score: 5 to 6), consider reducing the dose and/or frequency of dosing [see Use in Specific Populations (8.7) and Clinical Pharmacology (12.3)].

2.7 Dosage Adjustment in Patients with Renal Impairment

Consider reducing the dose and/or frequency of APLENZIN in patients with renal impairment (glomerular filtration rate less than 90 mL/min) [see Use in Specific Populations (8.6) and Clinical Pharmacology (12.3)].

2.8 Switching a Patient to or from a Monoamine Oxidase Inhibitor (MAOI) Antidepressant

At least 14 days should elapse between discontinuation of an MAOI intended to treat depression and initiation of therapy with APLENZIN. Conversely, at least 14 days should be allowed after stopping APLENZIN before starting an MAOI antidepressant [see Contraindications (4) and Drug Interactions (7.6)].

2.9 Use of APLENZIN with Reversible MAOIs such as Linezolid or Methylene Blue

Do not start APLENZIN in a patient who is being treated with a reversible MAOI such as linezolid or intravenous methylene blue. Drug interactions can increase risk of hypertensive reactions. In a patient who requires more urgent treatment of a psychiatric condition, non-pharmacological interventions, including hospitalization, should be considered [see Contraindications (4)].

In some cases, a patient already receiving APLENZIN therapy may require urgent treatment with linezolid or intravenous methylene blue. If acceptable alternatives to linezolid or intravenous methylene blue treatment are not available and the potential benefits of linezolid or intravenous methylene blue treatment are judged to outweigh the risks of hypertensive reactions in a particular patient, APLENZIN should be stopped promptly, and linezolid or intravenous methylene blue can be administered. The patient should be monitored for 2 weeks or until 24 hours after the last dose of linezolid or intravenous methylene blue, whichever comes first.

Therapy with APLENZIN may be resumed 24 hours after the last dose of linezolid or intravenous methylene blue.

The risk of administering methylene blue by non-intravenous routes (such as oral tablets or by local injection) or in intravenous doses much lower than 1 mg per kg with APLENZIN is unclear. The clinician should, nevertheless, be aware of the possibility of a drug interaction with such use [see Contraindications (4) and Drug Interactions (7.6)].

3 DOSAGE FORMS AND STRENGTHS

APLENZIN Extended-Release Tablets, 174 mg of bupropion hydrobromide, are white to off-white, round tablets printed on one side with black ink “BR” over “174”.

APLENZIN Extended-Release Tablets, 348 mg of bupropion hydrobromide, are white to off-white, round tablets printed on one side with black ink “BR” over “348”.

APLENZIN Extended-Release Tablets, 522 mg of bupropion hydrobromide, are white to off-white, round tablets printed on one side with black ink “BR” over “522”.

4 CONTRAINDICATIONS

- APLENZIN is contraindicated in patients with a seizure disorder.
- APLENZIN is contraindicated in patients with a current or prior diagnosis of bulimia or anorexia nervosa as a higher incidence of seizures was observed in such patients treated with APLENZIN [see Warnings and Precautions (5.3)].
- APLENZIN is contraindicated in patients undergoing abrupt discontinuation of alcohol, benzodiazepines, barbiturates, and antiepileptic drugs [see Warnings and Precautions (5.3) and Drug Interactions (7.3)].
- The use of MAOIs (intended to treat psychiatric disorders) concomitantly with APLENZIN or within 14 days of discontinuing treatment with APLENZIN is contraindicated. There is an increased risk of hypertensive reactions when APLENZIN is used concomitantly with MAOIs. The use of APLENZIN within 14 days of discontinuing treatment with an MAOI is also contraindicated. Starting APLENZIN in a patient treated with reversible MAOIs such as linezolid or intravenous methylene blue is contraindicated [see Dosage and Administration (2.5, 2.6, 2.9), Warnings and Precautions (5.4), and Drug Interactions (7.6)].
- APLENZIN is contraindicated in patients with known hypersensitivity to bupropion or other ingredients of APLENZIN. Anaphylactoid/anaphylactic reactions and Stevens-Johnson Syndrome have been reported [see Warnings and Precautions (5.8)].

5 WARNINGS AND PRECAUTIONS

5.1 Suicidal Thoughts and Behaviors in Children, Adolescents, and Young Adults

Patients with major depressive disorder (MDD), both adult and pediatric, may experience worsening of their depression and/or the emergence of suicidal ideation and behavior (suicidality) or unusual changes in behavior, whether or not they are taking antidepressant medications, and this risk may persist until significant remission occurs. Suicide is a known risk of depression and certain other psychiatric disorders, and these disorders themselves are the strongest predictors of suicide. There has been a long-standing concern that antidepressants may have a role in inducing worsening of depression and the emergence of suicidality in certain patients during the early phases of treatment.

Pooled analyses of short-term placebo-controlled trials of antidepressant drugs (Selective Serotonin Reuptake Inhibitors [SSRIs] and others) show that these drugs increase the risk of suicidal thinking and behavior (suicidality) in children, adolescents, and young adults (ages 18 to 24) with major depressive disorder (MDD) and other psychiatric disorders. Short-term studies did not show an increase in the risk of suicidality with antidepressants compared to placebo in adults beyond age 24; there was a reduction with antidepressants compared to placebo in adults aged 65 and older.

The pooled analyses of placebo-controlled trials in children and adolescents with MDD, obsessive compulsive disorder (OCD), or other psychiatric disorders included a total of 24 short-term trials of 9 antidepressant drugs in over 4,400 patients. The pooled analyses of placebo-controlled trials in adults with MDD or other psychiatric disorders included a total of 295 short-term trials (median duration of 2 months) of 11 antidepressant drugs in over 77,000 patients. There was considerable variation in risk of suicidality among drugs, but a tendency toward an increase in the younger patients for almost all drugs studied. There were differences in absolute risk of suicidality across the different indications, with the highest incidence in MDD. The risk differences (drug vs. placebo), however, were relatively stable within age strata and across indications. These risk differences (drug-placebo difference in the number of cases of suicidality per 1,000 patients treated) are provided in Table 2.

Table 2: Risk Differences in the Number of Suicidality Cases by Age Group in the Pooled Placebo-Controlled Trials of Antidepressants in Pediatric and Adult Patients
Age Range | Drug-Placebo Difference in Number of Cases of Suicidality per 1,000 Patients Treated
Increases Compared to Placebo
<18 years | 14 additional cases
18-24 years | 5 additional cases
Decreases Compared to Placebo
25-64 years | 1 fewer case
≥65 years | 6 fewer cases

No suicides occurred in any of the pediatric trials. There were suicides in the adult trials, but the number was not sufficient to reach any conclusion about drug effect on suicide.

It is unknown whether the suicidality risk extends to longer-term use, i.e., beyond several months. However, there is substantial evidence from placebo-controlled maintenance trials in adults with depression that the use of antidepressants can delay the recurrence of depression.

All patients being treated with antidepressants for any indication should be monitored appropriately and observed closely for clinical worsening, suicidality, and unusual changes in behavior, especially during the initial few months of a course of drug therapy, or at times of dose changes, either increases or decreases [see Boxed Warning and Use in Specific Populations (8.4)].

The following symptoms, anxiety, agitation, panic attacks, insomnia, irritability, hostility, aggressiveness, impulsivity, akathisia (psychomotor restlessness), hypomania, and mania, have been reported in adult and pediatric patients being treated with antidepressants for major depressive disorder as well as for other indications, both psychiatric and nonpsychiatric. Although a causal link between the emergence of such symptoms and either the worsening of depression and/or the emergence of suicidal impulses has not been established, there is concern that such symptoms may represent precursors to emerging suicidality.

Consideration should be given to changing the therapeutic regimen, including possibly discontinuing the medication, in patients whose depression is persistently worse, or who are experiencing emergent suicidality or symptoms that might be precursors to worsening depression or suicidality, especially if these symptoms are severe, abrupt in onset, or were not part of the patient’s presenting symptoms.

Families and caregivers of patients being treated with antidepressants for major depressive disorder or other indications, both psychiatric and nonpsychiatric, should be alerted about the need to monitor patients for the emergence of agitation, irritability, unusual changes in behavior, and the other symptoms described above, as well as the emergence of suicidality, and to report such symptoms immediately to healthcare providers. Such monitoring should include daily observation by families and caregivers. Prescriptions for APLENZIN should be written for the smallest quantity of tablets consistent with good patient management, in order to reduce the risk of overdose.

5.2 Neuropsychiatric Adverse Events and Suicide Risk in Smoking Cessation Treatment

APLENZIN is not approved for smoking cessation treatment; however, bupropion HCl sustained-release is approved for this use. Serious neuropsychiatric adverse events have been reported in patients taking bupropion for smoking cessation. These postmarketing reports have included changes in mood (including depression and mania), psychosis, hallucinations, paranoia, delusions, homicidal ideation, aggression, hostility, agitation, anxiety, and panic, as well as suicidal ideation, suicide attempt, and completed suicide [see Adverse Reactions (6.2)]. Some patients who stopped smoking may have been experiencing symptoms of nicotine withdrawal, including depressed mood. Depression, rarely including suicidal ideation, has been reported in smokers undergoing a smoking cessation attempt without medication. However, some of these adverse events occurred in patients taking bupropion who continued to smoke.

Neuropsychiatric adverse events occurred in patients without and with pre-existing psychiatric disease; some patients experienced worsening of their psychiatric illnesses. Observe patients for the occurrence of neuropsychiatric adverse events. Advise patients and caregivers that the patient should stop taking APLENZIN and contact a healthcare provider immediately if agitation, depressed mood, or changes in behavior or thinking that are not typical for the patient are observed, or if the patient develops suicidal ideation or suicidal behavior. The healthcare provider should evaluate the severity of the adverse events and the extent to which the patient is benefiting from treatment, and consider options including continued treatment under closer monitoring, or discontinuing treatment. In many postmarketing cases, resolution of symptoms after discontinuation of bupropion was reported. However, the symptoms persisted in some cases; therefore, ongoing monitoring and supportive care should be provided until symptoms resolve.

5.3 Seizure

APLENZIN can cause seizure. The risk of seizure is dose-related. The dose should not exceed 522 mg once daily. Increase the dose gradually. Discontinue APLENZIN and do not restart treatment if the patient experiences a seizure.

The risk of seizures is also related to patient factors, clinical situations, and concomitant medications that lower the seizure threshold. Consider these risks before initiating treatment with APLENZIN. APLENZIN is contraindicated in patients with a seizure disorder or conditions that increase the risk of seizure (e.g., severe head injury, arteriovenous malformation, CNS tumor or CNS infection, severe stroke, anorexia nervosa or bulimia, or abrupt discontinuation of alcohol, benzodiazepines, barbiturates, and antiepileptic drugs [see Contraindications (4)]. The following conditions can also increase the risk of seizure: concomitant use of other medications that lower the seizure threshold (e.g., other bupropion products, antipsychotics, tricyclic antidepressants, theophylline, and systemic corticosteroids), metabolic disorders (e.g., hypoglycemia, hyponatremia, severe hepatic impairment, and hypoxia), or use of illicit drugs (e.g., cocaine) or abuse or misuse of prescription drugs such as CNS stimulants. Additional predisposing conditions include diabetes mellitus treated with oral hypoglycemic drugs or insulin, use of anorectic drugs, excessive use of alcohol, benzodiazepines, sedative/hypnotics, or opiates.

Incidence of Seizure with Bupropion Use

The incidence of seizure with APLENZIN has not been formally evaluated in clinical trials. In studies using bupropion HCl sustained-release up to 300 mg per day (equivalent to APLENZIN 348 mg per day) the incidence of seizure was approximately 0.1% (1/1,000 patients). In a large prospective, follow-up study, the seizure incidence was approximately 0.4% (13/3,200) with bupropion HCl immediate-release in the range of 300 mg to 450 mg per day (equivalent to APLENZIN 348 mg to 522 mg per day).

Additional data accumulated for bupropion immediate-release suggests that the estimated seizure incidence increases almost tenfold between 450 and 600 mg/day (equivalent to APLENZIN 522 mg and 696 mg per day). The risk of seizure can be reduced if the APLENZIN dose does not exceed 522 mg once daily and the titration rate is gradual.

5.4 Hypertension

Treatment with APLENZIN can result in elevated blood pressure and hypertension. Assess blood pressure before initiating treatment with APLENZIN, and monitor periodically during treatment. The risk of hypertension is increased if APLENZIN is used concomitantly with MAOIs or other drugs that increase dopaminergic or noradrenergic activity [see Contraindications (4)].

Data from a comparative trial of the sustained-release formulation of bupropion HCl, nicotine transdermal system (NTS), the combination of sustained-release bupropion plus NTS, and placebo as an aid to smoking cessation suggest a higher incidence of treatment-emergent hypertension in patients treated with the combination of sustained-release bupropion and NTS. In this trial, 6.1% of subjects treated with the combination of sustained-release bupropion and NTS had treatment-emergent hypertension compared to 2.5%, 1.6%, and 3.1% of subjects treated with sustained-release bupropion, NTS, and placebo, respectively. The majority of these subjects had evidence of pre-existing hypertension. Three subjects (1.2%) treated with the combination of sustained-release bupropion and NTS and 1 subject (0.4%) treated with NTS had study medication discontinued due to hypertension compared with none of the subjects treated with sustained-release bupropion or placebo. Monitoring of blood pressure is recommended in patients who receive the combination of bupropion and nicotine replacement.

In the 3 trials of bupropion HCl extended-release in seasonal affective disorder, there were significant elevations in blood pressure. Hypertension was reported as an adverse reaction for 2% of the bupropion group (11/537) and none in the placebo group (0/511). In the SAD trials, 2 patients treated with bupropion discontinued from the study because they developed hypertension. None of the placebo group discontinued because of hypertension. The mean increase in systolic blood pressure was 1.3 mmHg in the bupropion group and 0.1 mmHg in the placebo group. The difference was statistically significant (p=0.013). The mean increase in diastolic blood pressure was 0.8 mmHg in the bupropion group and 0.1 mmHg in the placebo group. The difference was not statistically significant (p=0.075). In the SAD trials, 82% of patients were treated with 300 mg per day, and 18% were treated with 150 mg per day. The mean daily dose was 270 mg per day. The mean duration of bupropion exposure was 126 days.

In a clinical trial of bupropion immediate-release in MDD subjects with stable congestive heart failure (N=36), bupropion was associated with an exacerbation of pre-existing hypertension in 2 subjects, leading to discontinuation of bupropion treatment. There are no controlled studies assessing the safety of bupropion in patients with a recent history of myocardial infarction or unstable cardiac disease.

5.5 Activation of Mania/Hypomania

Antidepressant treatment can precipitate a manic, mixed, or hypomanic manic episode. The risk appears to be increased in patients with bipolar disorder or who have risk factors for bipolar disorder. Prior to initiating APLENZIN, screen patients for a history of bipolar disorder and the presence of risk factors for bipolar disorder (e.g., family history of bipolar disorder, suicide, or depression). APLENZIN is not approved for the treatment of bipolar depression.

5.6 Psychosis and Other Neuropsychiatric Reactions

Depressed patients treated with bupropion have had a variety of neuropsychiatric signs and symptoms, including delusions, hallucinations, psychosis, concentration disturbance, paranoia, and confusion. Some of these patients had a diagnosis of bipolar disorder. In some cases, these symptoms abated upon dose reduction and/or withdrawal of treatment. Discontinue APLENZIN if these reactions occur.

5.7 Angle-Closure Glaucoma

Angle-Closure Glaucoma: The pupillary dilation that occurs following use of many antidepressant drugs including APLENZIN may trigger an angle-closure attack in a patient with anatomically narrow angles who does not have a patent iridectomy.

5.8 Hypersensitivity Reactions

Anaphylactoid/anaphylactic reactions have occurred during clinical trials with bupropion. Reactions have been characterized by pruritus, urticaria, angioedema, and dyspnea, requiring medical treatment. In addition, there have been rare, spontaneous postmarketing reports of erythema multiforme, Stevens-Johnson Syndrome, and anaphylactic shock associated with bupropion. Instruct patients to discontinue APLENZIN and consult a healthcare provider if they develop an allergic or anaphylactoid/anaphylactic reaction (e.g., skin rash, pruritus, hives, chest pain, edema, and shortness of breath) during treatment.

There are reports of arthralgia, myalgia, fever with rash and other symptoms of serum sickness suggestive of delayed hypersensitivity.

6 ADVERSE REACTIONS

The following adverse reactions are discussed in greater detail in other sections of the labeling:

- Suicidal thoughts and behaviors in children, adolescents, and young adults [see Warnings and Precautions (5.1)]
- Neuropsychiatric adverse events and suicide risk in smoking cessation treatment [see Warnings and Precautions (5.2)]
- Seizure [see Warnings and Precautions (5.3)]
- Hypertension [see Warnings and Precautions (5.4)]
- Activation of mania or hypomania [see Warnings and Precautions (5.5)]
- Psychosis and other neuropsychiatric events [see Warnings and Precautions (5.6)]
- Angle-closure glaucoma [see Warnings and Precautions (5.7)]
- Hypersensitivity reactions [see Warnings and Precautions (5.8)]

6.1 Clinical Trials Experience

Because clinical trials are conducted under widely varying conditions, adverse reaction rates observed in the clinical trials of a drug cannot be directly compared to rates in the clinical trials of another drug and may not reflect the rates observed in practice.

Commonly Observed Adverse Reactions in Controlled Clinical Trials of Sustained-Release Bupropion Hydrochloride

Adverse reactions that occurred in at least 5% of patients treated with bupropion HCl sustained-release (300 mg and 400 mg per day) and at a rate at least twice the placebo rate are listed below.

300 mg/day of bupropion HCl sustained-release (equivalent to APLENZIN 348 mg/day): anorexia, dry mouth, rash, sweating, tinnitus, and tremor.

400 mg/day of bupropion HCl sustained-release (equivalent to APLENZIN 464 mg/day): abdominal pain, agitation, anxiety, dizziness, dry mouth, insomnia, myalgia, nausea, palpitation, pharyngitis, sweating, tinnitus, and urinary frequency.

APLENZIN is bioequivalent to bupropion HCl extended-release, which has been demonstrated to have similar bioavailability both to the immediate-release formulation of bupropion and to the sustained-release formulation of bupropion. The information included under this subsection and under subsection 6.2 is based primarily on data from controlled clinical trials with the sustained-release and extended-release formulations of bupropion hydrochloride.

Major Depressive Disorder

Adverse Reactions Leading to Discontinuation of Treatment with Bupropion HCl Immediate-Release, Bupropion HCl Sustained-Release, and Bupropion HCl Extended-Release in Major Depressive Disorder Trials

In placebo-controlled clinical trials with bupropion HCl sustained-release, 4%, 9%, and 11% of the placebo, 300 mg/day and 400 mg/day groups, respectively, discontinued treatment because of adverse reactions. The specific adverse reactions leading to discontinuation in at least 1% of the 300 mg/day or 400 mg/day groups and at a rate at least twice the placebo rate are listed in Table 3.

Table 3: Treatment Discontinuation Due to Adverse Reactions in Placebo-Controlled Trials in MDD
Adverse Reaction Term | Placebo (n=385) | Bupropion HCl Sustained-Release 300 mg/day [Equivalent to 348 mg/day bupropion HBr] (n=376) | Bupropion HCl Sustained-Release 400 mg/day [Equivalent to 464 mg/day bupropion HBr] (n=114)
Rash | 0.0% | 2.4% | 0.9%
Nausea | 0.3% | 0.8% | 1.8%
Agitation | 0.3% | 0.3% | 1.8%
Migraine | 0.3% | 0.0% | 1.8%

In clinical trials with bupropion HCl immediate-release, 10% of patients and volunteers discontinued due to an adverse reaction. Reactions resulting in discontinuation (in addition to those listed above for the sustained-release formulation) included vomiting, seizures, and sleep disturbances.

Adverse Reactions Occurring at an Incidence of >1% in Patients Treated with Bupropion HCl Immediate-Release or Bupropion HCl Sustained-Release in MDD

Table 4 summarizes the adverse reactions that occurred in placebo-controlled trials in patients treated with bupropion HCl sustained-release 300 mg/day and 400 mg/day. These include reactions that occurred in either the 300 mg or 400 mg group at an incidence of 1% or more and were more frequent than in the placebo group.

Table 4: Adverse Reactions in Placebo-Controlled Trials in Patients with MDD
Body System/Adverse Reaction | Placebo (n=385) | Bupropion HCl Sustained-Release 300 mg/day [Equivalent to 348 mg/day bupropion HBr] (n=376) | Bupropion HCl Sustained-Release 400 mg/day [Equivalent to 464 mg/day bupropion HBr] (n=114)
Body (General)
Headache | 23% | 26% | 25%
Infection | 6% | 8% | 9%
Abdominal pain | 2% | 3% | 9%
Asthenia | 2% | 2% | 4%
Chest pain | 1% | 3% | 4%
Pain | 2% | 2% | 3%
Fever | — [Hyphen denotes adverse reactions occurring in greater than 0 but less than 0.5% of patients] | 1% | 2%
Cardiovascular
Palpitation | 2% | 2% | 6%
Flushing | — | 1% | 4%
Migraine | 1% | 1% | 4%
Hot flashes | 1% | 1% | 3%
Digestive
Dry mouth | 7% | 17% | 24%
Nausea | 8% | 13% | 18%
Constipation | 7% | 10% | 5%
Diarrhea | 6% | 5% | 7%
Anorexia | 2% | 5% | 3%
Vomiting | 2% | 4% | 2%
Dysphagia | 0% | 0% | 2%
Musculoskeletal
Myalgia | 3% | 2% | 6%
Arthralgia | 1% | 1% | 4%
Arthritis | 0% | 0% | 2%
Twitch | — | 1% | 2%
Nervous System
Insomnia | 6% | 11% | 16%
Dizziness | 5% | 7% | 11%
Agitation | 2% | 3% | 9%
Anxiety | 3% | 5% | 6%
Tremor | 1% | 6% | 3%
Nervousness | 3% | 5% | 3%
Somnolence | 2% | 2% | 3%
Irritability | 2% | 3% | 2%
Memory decreased | 1% | — | 3%
Paresthesia | 1% | 1% | 2%
Central nervous system stimulation | 1% | 2% | 1%
Respiratory
Pharyngitis | 2% | 3% | 11%
Sinusitis | 2% | 3% | 1%
Increased cough | 1% | 1% | 2%
Skin
Sweating | 2% | 6% | 5%
Rash | 1% | 5% | 4%
Pruritus | 2% | 2% | 4%
Urticaria | 0% | 2% | 1%
Special Senses
Tinnitus | 2% | 6% | 6%
Taste perversion | — | 2% | 4%
Blurred vision or diplopia | 2% | 3% | 2%
Urogenital
Urinary frequency | 2% | 2% | 5%
Urinary urgency | 0% | — | 2%
Vaginal hemorrhage [Incidence based on the number of female patients.] | — | 0% | 2%
Urinary tract infection | — | 1% | 0%

The following additional adverse reactions occurred in controlled trials of bupropion HCl immediate-release (300 to 600 mg per day) at an incidence of at least 1% more frequently than in the placebo group were: cardiac arrhythmia (5% vs. 4%), hypertension (4% vs. 2%), hypotension (3% vs. 2%), tachycardia (11% vs. 9%), appetite increased (4% vs. 2%), dyspepsia (3% vs. 2%), menstrual complaints (5% vs. 1%), akathisia (2% vs. 1%), impaired sleep quality (4% vs. 2%), sensory disturbance (4% vs. 3%), confusion (8% vs. 5%), decreased libido (3% vs. 2%), hostility (6% vs. 4%), auditory disturbance (5% vs. 3%), and gustatory disturbance (3% vs. 1%).

Seasonal Affective Disorder

In placebo-controlled clinical trials in SAD, 9% of patients treated with bupropion HCl extended-release and 5% of patients treated with placebo discontinued treatment because of adverse reactions. The adverse reactions leading to discontinuation in at least 1% of patients treated with bupropion and at a rate numerically greater than the placebo rate were insomnia (2% vs. <1%) and headache (1% vs. <1%).

Table 5 summarizes the adverse reactions that occurred in patients treated with bupropion HCl extended-release for up to approximately 6 months in 3 placebo-controlled trials. These include reactions that occurred at an incidence of 2% or more and were more frequent than in the placebo group.

Table 5: Adverse Reactions in Placebo-Controlled Trials in Patients with SAD
System Organ Class/ Preferred Term | Placebo (n=511) | Bupropion HCl Extended-Release (n=537)
Gastrointestinal Disorder
Dry mouth | 15% | 26%
Nausea | 8% | 13%
Constipation | 2% | 9%
Flatulence | 3% | 6%
Abdominal pain | <1% | 2%
Nervous System Disorders
Headache | 26% | 34%
Dizziness | 5% | 6%
Tremor | <1% | 3%
Infections and Infestations
Nasopharyngitis | 12% | 13%
Upper respiratory tract infection | 8% | 9%
Sinusitis | 4% | 5%
Psychiatric Disorders
Insomnia | 13% | 20%
Anxiety | 5% | 7%
Abnormal dreams | 2% | 3%
Agitation | <1% | 2%
Musculoskeletal and Connective Tissue Disorders
Myalgia | 2% | 3%
Pain in extremity | 2% | 3%
Respiratory, Thoracic, and Mediastinal Disorders
Cough | 3% | 4%
General Disorders and Administration Site Conditions
Feeling jittery | 2% | 3%
Skin and Subcutaneous Tissue Disorders
Rash | 2% | 3%
Metabolism and Nutrition Disorders
Decreased appetite | 1% | 4%
Reproductive System and Breast Disorders
Dysmenorrhea | <1% | 2%
Ear and Labyrinth Disorders
Tinnitus | <1% | 3%
Vascular Disorders
Hypertension | 0% | 2%

Changes in Body Weight

Table 6 presents the incidence of body weight changes (≥5 lbs) in the short-term MDD trials using bupropion HCl sustained-release. There was a dose-related decrease in body weight.

Table 6: Incidence of Weight Gain or Weight Loss (≥5 lbs) in MDD Trials Using Bupropion HCl Sustained-Release
Weight Change | Bupropion HCl Sustained-Release 300 mg/day [Equivalent to 348 mg/day bupropion HBr] (n=339) | Bupropion HCl Sustained-Release 400 mg/day [Equivalent to 464 mg/day bupropion HBr] (n=112) | Placebo (n=347)
Gained >5 lbs | 3% | 2% | 4%
Lost >5 lbs | 14% | 19% | 6%

Table 7 presents the incidence of body weight changes (≥5 lbs) in the 3 SAD trials using bupropion HCl extended-release. A higher proportion of subjects in the bupropion group (23%) had a weight loss ≥5 lbs, compared to the placebo group (11%). These were relatively long-term trials (up to 6 months).

Table 7: Incidence of Weight Gain or Weight Loss (≥5 lbs) in SAD Trials Using Bupropion HCl Extended-Release
Weight Change | Bupropion HCl Extended-Release 150 to 300 mg/day (n=537) | Placebo (n=511)
Gained >5 lbs | 11% | 21%
Lost >5 lbs | 23% | 11%

6.2 Postmarketing Experience

The following adverse reactions have been identified during post-approval use of APLENZIN. Because these reactions are reported voluntarily from a population of uncertain size, it is not always possible to reliably estimate their frequency or establish a causal relationship to drug exposure.

Body (General)

Chills, facial edema, edema, peripheral edema, musculoskeletal chest pain, photosensitivity, and malaise.

Cardiovascular

Postural hypotension, stroke, vasodilation, syncope, complete atrioventricular block, extrasystoles, myocardial infarction, phlebitis, pulmonary embolism, and Brugada pattern/syndrome.

Digestive

Abnormal liver function, bruxism, gastric reflux, gingivitis, glossitis, increased salivation, jaundice, mouth ulcers, stomatitis, thirst, edema of tongue, colitis, esophagitis, gastrointestinal hemorrhage, gum hemorrhage, hepatitis, intestinal perforation, liver damage, pancreatitis, and stomach ulcer.

Endocrine

Hyperglycemia, hypoglycemia, and syndrome of inappropriate antidiuretic hormone secretion.

Hemic and Lymphatic

Ecchymosis, anemia, leukocytosis, leukopenia, lymphadenopathy, pancytopenia, and thrombocytopenia. Altered PT and/or INR, associated with hemorrhagic or thrombotic complications, were observed when bupropion was coadministered with warfarin.

Metabolic and Nutritional

Glycosuria.

Musculoskeletal

Leg cramps, fever/rhabdomyolysis, and muscle weakness.

Nervous System

Abnormal coordination, depersonalization, emotional lability, hyperkinesia, hypertonia, hypesthesia, vertigo, amnesia, ataxia, derealization, abnormal electroencephalogram (EEG), aggression, akinesia, aphasia, coma, dysarthria, dyskinesia, dystonia, euphoria, extrapyramidal syndrome, hypokinesia, increased libido, neuralgia, neuropathy, paranoid ideation, restlessness, suicide attempt, unmasking tardive dyskinesia and aseptic meningitis.

Respiratory

Bronchospasm and pneumonia.

Skin and Subcutaneous Tissue Disorders

Maculopapular rash, alopecia, angioedema, exfoliative dermatitis, hirsutism, acute generalized exanthematous pustulosis and drug reaction with eosinophilia and systemic symptoms (DRESS).

Special Senses

Accommodation abnormality, dry eye, deafness, increased intraocular pressure, angle-closure glaucoma, and mydriasis.

Urogenital

Impotence, polyuria, prostate disorder, abnormal ejaculation, cystitis, dyspareunia, dysuria, gynecomastia, menopause, painful erection, salpingitis, urinary incontinence, urinary retention, and vaginitis.

7 DRUG INTERACTIONS

7.1 Potential for Other Drugs to Affect APLENZIN

Bupropion is primarily metabolized to hydroxybupropion by CYP2B6. Therefore, the potential exists for drug interactions between APLENZIN and drugs that are inhibitors or inducers of CYP2B6.

Inhibitors of CYP2B6

Ticlopidine and Clopidogrel: Concomitant treatment with these drugs can increase bupropion exposures but decrease hydroxybupropion exposure. Based on clinical response, dosage adjustment of APLENZIN may be necessary when coadministered with CYP2B6 inhibitors (e.g., ticlopidine or clopidogrel) [see Clinical Pharmacology (12.3)].

Inducers of CYP2B6

Ritonavir, Lopinavir, and Efavirenz: Concomitant treatment with these drugs can decrease bupropion and hydroxybupropion exposure. Dosage increase of APLENZIN may be necessary when coadministered with ritonavir, lopinavir, or efavirenz but should not exceed the maximum recommended dose [see Clinical Pharmacology (12.3)].

Carbamazepine, Phenobarbital, Phenytoin: While not systemically studied, these drugs may induce metabolism of bupropion and may decrease bupropion exposure [see Clinical Pharmacology (12.3)]. If bupropion is used concomitantly with a CYP inducer, it may be necessary to increase the dose of bupropion, but the maximum recommended dose should not be exceeded.

7.2 Potential for APLENZIN to Affect Other Drugs

Drugs Metabolized by CYP2D6

Bupropion and its metabolites (erythrohydrobupropion, threohydrobupropion, hydroxybupropion) are CYP2D6 inhibitors. Therefore, coadministration of APLENZIN with drugs that are metabolized by CYP2D6 can increase the exposures of drugs that are substrates of CYP2D6. Such drugs include certain antidepressants (e.g., venlafaxine, nortriptyline, imipramine, desipramine, paroxetine, fluoxetine, and sertraline), antipsychotics (e.g., haloperidol, risperidone, and thioridazine), beta-blockers (e.g., metoprolol), and Type 1C antiarrhythmics (e.g., propafenone, and flecainide). When used concomitantly with APLENZIN, it may be necessary to decrease the dose of these CYP2D6 substrates, particularly for drugs with a narrow therapeutic index.

Drugs that require metabolic activation by CYP2D6 to be effective (e.g., tamoxifen), theoretically could have reduced efficacy when administered concomitantly with inhibitors of CYP2D6 such as bupropion. Patients treated concomitantly with APLENZIN and such drugs may require increased doses of the drug [see Clinical Pharmacology (12.3)].

7.3 Drugs That Lower Seizure Threshold

Use extreme caution when coadministering APLENZIN with other drugs that lower the seizure threshold (e.g., other bupropion products, antipsychotics, antidepressants, theophylline, or systemic corticosteroids). Use low initial doses of APLENZIN and increase the dose gradually [see Warnings and Precautions (5.3)].

7.4 Dopaminergic Drugs (Levodopa and Amantadine)

Bupropion, levodopa, and amantadine have dopamine agonist effects. CNS toxicity has been reported when bupropion was coadministered with levodopa or amantadine. Adverse reactions have included restlessness, agitation, tremor, ataxia, gait disturbance, vertigo, and dizziness. It is presumed that the toxicity results from cumulative dopamine agonist effects. Use caution when administering APLENZIN concomitantly with these drugs.

7.5 Use with Alcohol

In postmarketing experience, there have been rare reports of adverse neuropsychiatric events or reduced alcohol tolerance in patients who were drinking alcohol during treatment with APLENZIN. The consumption of alcohol during treatment with APLENZIN should be minimized or avoided.

7.6 MAO Inhibitors

Bupropion inhibits the reuptake of dopamine and norepinephrine. Concomitant use of MAOIs and bupropion is contraindicated because there is an increased risk of hypertensive reactions if bupropion is used concomitantly with MAOIs. Studies in animals demonstrate that the acute toxicity of bupropion is enhanced by the MAO inhibitor phenelzine. At least 14 days should elapse between discontinuation of an MAOI intended to treat depression and initiation of treatment with APLENZIN. Conversely, at least 14 days should be allowed after stopping APLENZIN before starting an MAOI antidepressant [see Dosage and Administration (2.8, 2.9) and Contraindications (4)].

7.7 Drug-Laboratory Test Interactions

False-positive urine immunoassay screening tests for amphetamines have been reported in patients taking bupropion. This is due to lack of specificity of some screening tests. False-positive test results may result even following discontinuation of bupropion therapy. Confirmatory tests, such as gas chromatography/mass spectrometry, will distinguish bupropion from amphetamines.

8 USE IN SPECIFIC POPULATIONS

8.1 Pregnancy

Pregnancy Exposure Registry

There is a pregnancy exposure registry that monitors pregnancy outcomes in women exposed to antidepressants during pregnancy. Healthcare providers are encouraged to register patients by calling the National Pregnancy Registry for Antidepressants at 1-844-405-6185 or visiting online at https://womensmentalhealth.org/clinical-and-research-programs/pregnancyregistry/antidepressants/.

Risk Summary

Data from epidemiological studies of pregnant women exposed to bupropion in the first trimester have not identified an increased risk of congenital malformations overall (see Data). There are risks to the mother associated with untreated depression (see Clinical Considerations). When bupropion was administered to pregnant rats during organogenesis, there was no evidence of fetal malformations at doses up to approximately 10 times the maximum recommended human dose (MRHD) of 450 mg/day. When given to pregnant rabbits during organogenesis, non-dose-related increases in incidence of fetal malformations and skeletal variations were observed at doses approximately equal to the MRHD and greater. Decreased fetal weights were seen at doses twice the MRHD and greater (see Data).

The estimated background risk for major birth defects and miscarriage are unknown for the indicated population. All pregnancies have a background rate of birth defect, loss, or other adverse outcomes. In the U.S. general population, the estimated background risk of major birth defects and miscarriage in clinically recognized pregnancies is 2% to 4% and 15% to 20%, respectively.

Clinical Considerations

Disease-associated maternal and/or embryo/fetal risk

A prospective, longitudinal study followed 201 pregnant women with a history of major depressive disorder who were euthymic and taking antidepressants during pregnancy at the beginning of pregnancy. The women who discontinued antidepressants during pregnancy were more likely to experience a relapse of major depression than women who continued antidepressants. Consider the risks to the mother of untreated depression and potential effects on the fetus when discontinuing or changing treatment with antidepressant medications during pregnancy and postpartum.

Data

Human Data

Data from the international bupropion Pregnancy Registry (675 first trimester exposures) and a retrospective cohort study using the United Healthcare database (1,213 first trimester exposures) did not show an increased risk for malformations overall. The Registry was not designed or powered to evaluate specific defects but suggested a possible increase in cardiac malformations.

No increased risk for cardiovascular malformations overall has been observed after bupropion exposure during the first trimester. The prospectively observed rate of cardiovascular malformations in pregnancies with exposure to bupropion in the first trimester from the international Pregnancy Registry was 1.3% (9 cardiovascular malformations/675 first-trimester maternal bupropion exposures), which is similar to the background rate of cardiovascular malformations (approximately 1%). Data from the United Healthcare database, which has a limited number of exposed cases with cardiovascular malformations, and a case-controlled study (6,853 infants with cardiovascular malformations and 5,753 with non-cardiovascular malformations) from the National Birth Defects Prevention Study (NBDPS) did not show an increased risk for cardiovascular malformations overall after bupropion exposure during the first trimester.

Study findings on bupropion exposure during the first trimester and risk left ventricular outflow tract obstruction (LVOTO) are inconsistent and do not allow conclusions regarding possible association. The United Healthcare database lacked sufficient power to evaluate this association; the NBDPS found increased risk for LVOTO (n = 10; adjusted odds ratio (OR) = 2.6; 95% CI 1.2, 5.7) and the Slone Epidemiology case control study did not find increased risk for LVOTO.

Study findings on bupropion exposure during the first trimester and risk for ventricular septal defect (VSD) are inconsistent and do not allow conclusions regarding a possible association. The Slone Epidemiology Study found an increased risk for VSD following first trimester maternal bupropion exposure (n = 17; adjusted OR = 2.5; 95% CI: 1.3, 5.0) but did not find an increased risk for any other cardiovascular malformations studied (including LVOTO as above). The NBDPS and United Healthcare database study did not find an association between first trimester maternal bupropion exposure and VSD.

For the findings of LVOTO and VSD, the studies were limited by the small number of exposed cases, inconsistent findings among studies, and the potential for chance findings from multiple comparisons in case control studies.

Animal Data

In studies conducted in pregnant rats and rabbits, bupropion was administered orally during the period of organogenesis at doses of up to 450 and 150 mg/kg/day, respectively (approximately 10 and 6 times the MRHD, respectively, on a mg/m^2 basis). There was no evidence of fetal malformations in rats. When given to pregnant rabbits during organogenesis, non-dose-related increases in incidence of fetal malformations and skeletal variations were observed at the lowest dose tested (25 mg/kg/day, approximately equal to the MRHD on a mg/m^2 basis) and greater. Decreased fetal weights were observed at 50 mg/kg (approximately 2 times the MRHD on a mg/m^2 basis) and greater. No maternal toxicity was evident at doses of 50/mg/kg/day or less.

In a pre- and postnatal development study, bupropion administered orally to pregnant rats at doses of up to 150 mg/kg/day (approximately 6 times the MRHD on a mg/m^2 basis) from embryonic implantation through lactation, had no effect on pup growth or development.

8.2 Lactation

Risk Summary

Data from published literature report the presence of bupropion and its metabolites in human milk (see Data). There are no data on the effects of bupropion or its metabolites on milk production. Limited data from postmarketing reports have not identified a clear association of adverse reactions in the breastfed infant. The developmental and health benefits of breastfeeding should be considered along with the mother’s clinical need for APLENZIN and any potential adverse effects on the breastfed child from APLENZIN or from the underlying maternal condition.

Data

In a lactation study of ten women, levels of orally dosed bupropion and its active metabolites were measured in expressed milk. The average daily infant exposure (assuming 150 mL/kg daily consumption) to bupropion and its active metabolites was 2% of the maternal weight-adjusted dose. Postmarketing reports have described seizures in breastfed infants. The relationship of bupropion exposure and these seizures is unclear.

8.4 Pediatric Use

Safety and effectiveness in the pediatric population have not been established. When considering the use of APLENZIN in a child or adolescent, balance the potential risks with the clinical need [see Boxed Warning and Warnings and Precautions (5.1)].

8.5 Geriatric Use

Of the approximately 6,000 patients who participated in clinical trials with bupropion hydrochloride sustained-release tablets (depression and smoking cessation studies), 275 were ≥65 years old and 47 were ≥75 years old. In addition, several hundred patients ≥65 years of age participated in clinical trials using the immediate-release formulation of bupropion hydrochloride (depression studies). No overall differences in safety or effectiveness were observed between these subjects and younger subjects. Reported clinical experience has not identified differences in responses between the elderly and younger patients, but greater sensitivity of some older individuals cannot be ruled out.

Bupropion is extensively metabolized in the liver to active metabolites, which are further metabolized and excreted by the kidneys. The risk of adverse reactions may be greater in patients with impaired renal function. Because elderly patients are more likely to have decreased renal function, it may be necessary to consider this factor in dose selection; it may be useful to monitor renal function [see Dosage and Administration (2.7), Use in Specific Populations (8.6), and Clinical Pharmacology (12.3)].

8.6 Renal Impairment

Consider a reduced dose and/or dosing frequency of APLENZIN in patients with renal impairment (glomerular filtration rate: <90 mL/min). Bupropion and its metabolites are cleared renally and may accumulate in such patients to a greater extent than usual. Monitor closely for adverse reactions that could indicate high bupropion or metabolite exposures [see Dosage and Administration (2.7) and Clinical Pharmacology (12.3)].

8.7 Hepatic Impairment

In patients with moderate to severe hepatic impairment (Child-Pugh score: 7 to 15), the maximum APLENZIN dose is 174 mg every other day. In patients with mild hepatic impairment (Child-Pugh score: 5 to 6), consider reducing the dose and/or frequency of dosing [see Dosage and Administration (2.6) and Clinical Pharmacology (12.3)].

9 DRUG ABUSE AND DEPENDENCE

9.1 Controlled Substance

Bupropion is not a controlled substance.

9.2 Abuse

Humans

Controlled clinical studies of bupropion HCl immediate-release conducted in normal volunteers, in subjects with a history of multiple drug abuse, and in depressed patients demonstrated an increase in motor activity and agitation/excitement.

In a population of individuals experienced with drugs of abuse, a single dose of 400 mg bupropion produced mild amphetamine-like activity as compared to placebo on the Morphine-Benzedrine Subscale of the Addiction Research Center Inventories (ARCI), and a score intermediate between placebo and amphetamine on the Liking Scale of the ARCI. These scales measure general feelings of euphoria and drug desirability.

Findings in clinical trials, however, are not known to reliably predict the abuse potential of drugs. Nonetheless, evidence from single-dose studies does suggest that the recommended daily dosage of bupropion when administered in divided doses is not likely to be significantly reinforcing to amphetamine or CNS stimulant abusers. However, higher doses (that could not be tested because of the risk of seizure) might be modestly attractive to those who abuse CNS stimulant drugs.

Bupropion hydrochloride extended-release tablets are intended for oral use only. The inhalation of crushed tablets or injection of dissolved bupropion has been reported. Seizures and/or cases of death have been reported when bupropion has been administered intranasally or by parenteral injection.

Animals

Studies in rodents and primates demonstrated that bupropion exhibits some pharmacologic actions common to psychostimulants. In rodents, it has been shown to increase locomotor activity, elicit a mild stereotyped behavioral response, and increase rates of responding in several schedule-controlled behavior paradigms. In primate models assessing the positive reinforcing effects of psychoactive drugs, bupropion was self-administered intravenously. In rats, bupropion produced amphetamine-like and cocaine-like discriminative stimulus effects in drug discrimination paradigms used to characterize the subjective effects of psychoactive drugs.

10 OVERDOSAGE

10.1 Human Overdose Experience

Overdoses of up to 30 grams or more of bupropion have been reported. Seizure was reported in approximately one third of all cases. Other serious reactions reported with overdoses of bupropion alone included hallucinations, loss of consciousness, mental status changes, sinus tachycardia, ECG changes such as conduction disturbances or arrhythmias, clonus, myoclonus, and hyperreflexia. Fever, muscle rigidity, rhabdomyolysis, hypotension, stupor, coma, and respiratory failure have been reported mainly when bupropion was part of multiple drug overdoses.

Although most patients recovered without sequelae, deaths associated with overdoses of bupropion alone have been reported in patients ingesting large doses of the drug. Multiple uncontrolled seizures, bradycardia, cardiac failure, and cardiac arrest prior to death were reported in these patients.

10.2 Overdosage Management

Consult a Certified Poison Control Center for up-to-date guidance and advice. Call 1-800-222-1222 or refer to www.poison.org.

There are no known antidotes for bupropion. In case of an overdose, provide supportive care, including close medical supervision and monitoring. Consider the possibility of multiple drug overdose.

11 DESCRIPTION

APLENZIN® (bupropion hydrobromide), an antidepressant of the aminoketone class, is chemically unrelated to tricyclic, tetracyclic, selective serotonin reuptake inhibitor, or other known antidepressant agents. Its structure closely resembles that of diethylpropion; it is related to phenylethylamines. It is designated as (±)-2-(tert-butylamino)-3’-chloropropiophenone hydrobromide. The molecular weight is 320.6. The molecular formula is C13H18ClNO•HBr. Bupropion hydrobromide powder is white or almost white, crystalline, and soluble in water. It has a bitter taste and produces the sensation of local anesthesia on the oral mucosa. The structural formula is:

APLENZIN tablets are supplied for oral administration as 174 mg, 348 mg, and 522 mg white to off-white extended-release tablets. Each tablet contains the labeled amount of bupropion hydrobromide and the inactive ingredients: ethylcellulose, glyceryl dibehenate, polyvinyl alcohol, polyethylene glycol, povidone, and dibutyl sebacate. Carnauba wax is included in the 174 mg and 348 mg strengths. The tablets are printed with edible black ink.

The insoluble shell of the extended-release tablet may remain intact during gastrointestinal transit and is eliminated in the feces.

12 CLINICAL PHARMACOLOGY

12.1 Mechanism of Action

The mechanism of action of bupropion is unknown, as is the case with other antidepressants. However, it is presumed that this action is mediated by noradrenergic and/or dopaminergic mechanisms. Bupropion is a relatively weak inhibitor of the neuronal uptake of norepinephrine and dopamine and does not inhibit monoamine oxidase or the reuptake of serotonin.

12.3 Pharmacokinetics

Bupropion is a racemic mixture. The pharmacologic activity and pharmacokinetics of the individual enantiomers have not been studied.

Following chronic dosing of APLENZIN 348 mg once-daily tablets, the mean peak steady-state plasma concentration and area under the curve of bupropion were 134.3 (±38.2) ng/mL and 1409 (±346) ng•hr/mL, respectively. Steady-state plasma concentrations of bupropion were reached within 8 days. The elimination half-life (±SD) of bupropion after a single dose is 21.3 (±6.7) hours.

In a study comparing 10-day dosing with APLENZIN 348 mg once-daily and bupropion HCl extended-release 300 mg once-daily, (following a 3-day titration with bupropion HCl extended-release 150 mg once-daily), APLENZIN peak plasma concentration and area under the curve for bupropion and the 3 metabolites (hydroxybupropion, threohydrobupropion, and erythrohydrobupropion) were equivalent to bupropion HCl extended-release 300 mg, with the average being 8 to 14% lower.

In a single-dose study, two APLENZIN tablets 174 mg once-daily and one APLENZIN tablet 348 mg once-daily were evaluated. Equivalence was demonstrated for peak plasma concentration and area under the curve for bupropion and the 3 metabolites.

A multidose study compared 14-day dosing with APLENZIN tablets 522 mg once-daily to dosing with three APLENZIN tablets 174 mg once-daily, following a 3-day titration with one APLENZIN tablet 174 mg once-daily, and a succeeding 5-day titration with two APLENZIN tablets 174 mg once-daily. Equivalence was demonstrated for peak plasma concentration and area under the curve for bupropion and the 3 metabolites.

These findings demonstrate that APLENZIN tablets 174 mg, 348 mg, and 522 mg are dose proportional.

Absorption

Following single oral administration of APLENZIN tablets to healthy volunteers, the median time to peak plasma concentrations for bupropion was approximately 5 hours. The presence of food did not affect the peak concentration and time to peak plasma concentration of bupropion; the area under the curve was increased by 19%.

Distribution

In vitro tests demonstrated that bupropion is 84% bound to human plasma proteins at concentrations up to 200 mcg/mL. The extent of protein binding of the hydroxybupropion metabolite is similar to that for bupropion, whereas the extent of protein binding of the threohydrobupropion metabolite is about half that of bupropion.

Metabolism

Bupropion is extensively metabolized in humans. Three metabolites are active: hydroxybupropion, which is formed via hydroxylation of the tert-butyl group of bupropion, and the amino-alcohol isomers threohydrobupropion and erythrohydrobupropion, which are formed via reduction of the carbonyl group. In vitro findings suggest that CYP2B6 is the principal isoenzyme involved in the formation of hydroxybupropion, while cytochrome P450 enzymes are not involved in the formation of threohydrobupropion. Oxidation of the bupropion side chain results in the formation of a glycine conjugate of meta-chlorobenzoic acid, which is then excreted as the major urinary metabolite. The potency and toxicity of the metabolites relative to bupropion have not been fully characterized. However, it has been demonstrated in an antidepressant screening test in mice that hydroxybupropion is one half as potent as bupropion, while threohydrobupropion and erythrohydrobupropion are 5-fold less potent than bupropion. This may be of clinical importance, because the plasma concentrations of the metabolites are as high or higher than those of bupropion.

At steady state, peak plasma concentration of hydroxybupropion occurred approximately 6 hours after administration of APLENZIN, and it was approximately 9 times the peak level of the parent drug. The elimination half-life of hydroxybupropion is approximately 24.3 (±4.9) hours, and its AUC at steady state is about 15.6 times that of bupropion. The times to peak concentrations for the erythrohydrobupropion and threohydrobupropion metabolites are similar to that of hydroxybupropion. However, the elimination half-lives of erythrohydrobupropion and threohydrobupropion are longer, approximately 31.1(±7.8) and 50.8 (±8.5) hours, respectively, and steady-state AUCs were 1.5 and 6.8 times that of bupropion, respectively.

Bupropion and its metabolites exhibit linear kinetics following chronic administration of 300 mg to 450 mg/day of bupropion hydrochloride (equivalent to 348 mg and 522 mg of APLENZIN, respectively).

Elimination

Following oral administration of 200 mg of ^14C-bupropion in humans, 87% and 10% of the radioactive dose were recovered in the urine and feces, respectively. Only 0.5% of the oral dose was excreted as unchanged bupropion.

Specific Populations

Factors or conditions altering metabolic capacity (e.g., liver disease, congestive heart failure [CHF], age, concomitant medications, etc.) or elimination may be expected to influence the degree and extent of accumulation of the active metabolites of bupropion. The elimination of the major metabolites of bupropion may be affected by reduced renal or hepatic function, because they are moderately polar compounds and are likely to undergo further metabolism or conjugation in the liver prior to urinary excretion.

Patients with Renal Impairment

There is limited information on the pharmacokinetics of bupropion in patients with renal impairment. An inter-trial comparison between normal subjects and subjects with end-stage renal failure demonstrated that the parent drug Cmax and AUC values were comparable in the 2 groups, whereas the hydroxybupropion and threohydrobupropion metabolites had a 2.3- and 2.8-fold increase, respectively, in AUC for subjects with end-stage renal failure. A second study, comparing normal subjects and subjects with moderate-to-severe renal impairment (GFR 30.9 ± 10.8 mL/min) showed that after a single 150 mg dose of sustained-release bupropion, exposure to bupropion was approximately 2-fold higher in subjects with impaired renal function, while levels of the hydroxybupropion and threo/erythrohydrobupropion (combined) metabolites were similar in the 2 groups. Bupropion is extensively metabolized in the liver to active metabolites, which are further metabolized and subsequently excreted by the kidneys. The elimination of the major metabolites of bupropion may be reduced by impaired renal function. APLENZIN should be used with caution in patients with renal impairment, and a reduced frequency and/or dose should be considered [see Dosage and Administration (2.7) and Use in Specific Populations (8.6)].

Patients with Hepatic Impairment

The effect of hepatic impairment on the pharmacokinetics of bupropion was characterized in 2 single-dose trials, one in subjects with alcoholic liver disease and one in subjects with mild to severe cirrhosis. The first trial demonstrated that the half-life of hydroxybupropion was significantly longer in 8 subjects with alcoholic liver disease than in 8 healthy volunteers (32±14 hours versus 21±5 hours, respectively). Although not statistically significant, the AUCs for bupropion and hydroxybupropion were more variable and tended to be greater (by 53% to 57%) in patients with alcoholic liver disease. The differences in half-life for bupropion and the other metabolites in the 2 groups were minimal.

The second trial demonstrated no statistically significant differences in the pharmacokinetics of bupropion and its active metabolites in 9 subjects with mild to moderate hepatic cirrhosis compared to 8 healthy volunteers. However, more variability was observed in some of the pharmacokinetic parameters for bupropion (AUC, Cmax, and Tmax) and its active metabolites (t½) in subjects with mild to moderate hepatic cirrhosis. In addition, in patients with severe hepatic cirrhosis, the bupropion Cmax and AUC were substantially increased (mean difference: by approximately 70% and 3-fold, respectively) and more variable when compared to values in healthy volunteers; the mean bupropion half-life was also longer (29 hours in subjects with severe hepatic cirrhosis vs. 19 hours in healthy subjects). For the metabolite hydroxybupropion, the mean Cmax was approximately 69% lower. For the combined amino-alcohol isomers threohydrobupropion and erythrohydrobupropion, the mean Cmax was approximately 31% lower. The mean AUC increased by about 1½-fold for hydroxybupropion and about 2½-fold for threo/erythrohydrobupropion. The median Tmax was observed 19 hours later for hydroxybupropion and 31 hours later for threo/erythrohydrobupropion. The mean half-lives for hydroxybupropion and threo/erythrohydrobupropion were increased 5- and 2-fold, respectively, in patients with severe hepatic cirrhosis compared to healthy volunteers [see Dosage and Administration (2.6) and Use in Specific Populations (8.7)].

Left Ventricular Dysfunction

During a chronic dosing study with bupropion in 14 depressed patients with left ventricular dysfunction (history of CHF or an enlarged heart on x-ray), there was no apparent effect on the pharmacokinetics of bupropion or its metabolites, compared to healthy volunteers.

Age

The effects of age on the pharmacokinetics of bupropion and its metabolites have not been fully characterized, but an exploration of steady-state bupropion concentrations from several depression efficacy studies involving patients dosed in a range of 300 to 750 mg/day, on a 3 times daily schedule, revealed no relationship between age (18 to 83 years) and plasma concentration of bupropion. A single-dose pharmacokinetic study demonstrated that the disposition of bupropion and its metabolites in elderly subjects was similar to that in younger subjects. These data suggest that there is no prominent effect of age on bupropion concentration; however, another single- and multiple-dose pharmacokinetic study suggested that the elderly are at increased risk for accumulation of bupropion and its metabolites [see Use in Specific Populations (8.5)].

Gender

A single-dose study involving 12 healthy male and 12 healthy female volunteers revealed no sex-related differences in the pharmacokinetic parameters of bupropion. In addition, pooled analysis of bupropion pharmacokinetic data from 90 healthy male and 90 healthy female volunteers revealed no sex-related differences in the peak plasma concentrations of bupropion. The mean systemic exposure (AUC) was approximately 13% higher in male volunteers compared to female volunteers.

Smokers

The effects of cigarette smoking on the pharmacokinetics of bupropion hydrochloride were studied in 34 healthy male and female volunteers; 17 were chronic cigarette smokers and 17 were nonsmokers. Following oral administration of a single 150 mg dose of bupropion, there was no statistically significant difference in Cmax, half-life, Tmax, AUC, or clearance of bupropion or its active metabolites between smokers and nonsmokers.

Drug Interactions

Potential for Other Drugs to Affect APLENZIN

In vitro studies indicate that bupropion is primarily metabolized to hydroxybupropion by CYP2B6. Therefore, the potential exists for drug interactions between APLENZIN and drugs that are inhibitors or inducers of CYP2B6. In addition, in vitro studies suggest that paroxetine, sertraline, norfluoxetine, fluvoxamine, and nelfinavir inhibit the hydroxylation of bupropion.

Inhibitors of CYP2B6

Ticlopidine, Clopidogrel: In a study in healthy male volunteers, clopidogrel 75 mg once daily or ticlopidine 250 mg twice daily increased exposures (Cmax and AUC) of bupropion by 40% and 60% for clopidogrel, by 38% and 85% for ticlopidine, respectively. The exposures of hydroxybupropion were decreased.

Prasugrel: In healthy subjects, prasugrel increased bupropion Cmax and AUC values by 14% and 18%, respectively, and decreased Cmax and AUC values of hydroxybupropion by 32% and 24%, respectively.

Cimetidine: Following oral administration of bupropion 300 mg with and without cimetidine 800 mg in 24 healthy young male volunteers, the pharmacokinetics of bupropion and hydroxybupropion were unaffected. However, there were 16% and 32% increases in the AUC and Cmax, respectively, of the combined moieties of threohydrobupropion and erythrohydrobupropion.

Citalopram: Citalopram did not affect the pharmacokinetics of bupropion and its three metabolites.

Inducers of CYP2B6

Ritonavir and Lopinavir: In a healthy volunteer study, ritonavir 100 mg twice daily reduced the AUC and Cmax of bupropion by 22% and 21%, respectively. The exposure of the hydroxybupropion metabolite was decreased by 23%, the threohydrobupropion decreased by 38%, and the erythrohydrobupropion decreased by 48%. In a second healthy volunteer study, ritonavir 600 mg twice daily decreased the AUC and Cmax of bupropion by 66% and 62%, respectively. The exposure of the hydroxybupropion metabolite was decreased by 78%, the threohydrobupropion decreased by 50%, and the erythrohydrobupropion decreased by 68%.

In another healthy volunteer study, lopinavir 400 mg/ritonavir 100 mg twice daily decreased bupropion AUC and Cmax by 57%. The AUC and Cmax of hydroxybupropion metabolite were decreased by 50% and 31%, respectively.

Efavirenz: In a study of healthy volunteers, efavirenz 600 mg once daily for 2 weeks reduced the AUC and Cmax of bupropion by approximately 55% and 34%, respectively. The AUC of hydroxybupropion was unchanged, whereas Cmax of hydroxybupropion was increased by 50%.

Carbamazepine, Phenobarbital, Phenytoin: While not systematically studied, these drugs may induce the metabolism of bupropion.

Potential for APLENZIN to Affect Other Drugs

Animal data indicated that bupropion may be an inducer of drug-metabolizing enzymes in humans. In a study of 8 healthy male volunteers, following a 14-day administration of bupropion 100 mg three times per day, there was no evidence of induction of its own metabolism. Nevertheless, there may be the potential for clinically important alterations of blood levels of coadministered drugs.

Drugs Metabolized by CYP2D6

In vitro, bupropion and hydroxybupropion are CYP2D6 inhibitors. In a clinical study of 15 male subjects (ages 19 to 35 years) who were extensive metabolizers of CYP2D6, bupropion given as 150 mg twice daily followed by a single dose of 50 mg desipramine increased the Cmax, AUC, and T½ of desipramine by an average of approximately 2-, 5-, and 2-fold, respectively. The effect was present for at least 7 days after the last dose of bupropion. Concomitant use of bupropion with other drugs metabolized by CYP2D6 has not been formally studied.

Citalopram: Although citalopram is not primarily metabolized by CYP2D6, in one study bupropion increased the Cmax and AUC of citalopram by 30% and 40%, respectively.

Lamotrigine: Multiple oral doses of bupropion had no statistically significant effects on the single-dose pharmacokinetics of lamotrigine in 12 healthy volunteers.

13 NONCLINICAL TOXICOLOGY

13.1 Carcinogenesis, Mutagenesis, Impairment of Fertility

Carcinogenesis

Lifetime carcinogenicity studies were performed in rats and mice at doses up to 300 and 150 mg/kg/day bupropion hydrochloride, respectively. These doses are approximately 6 and 2 times the maximum recommended human dose (MRHD), respectively, on a mg/m^2 basis. In the rat study there was an increase in nodular proliferative lesions of the liver at doses of 100 to 300 mg/kg/day of bupropion hydrochloride (approximately 2 to 6 times the MRHD on a mg/m^2 basis); lower doses were not tested. The question of whether or not such lesions may be precursors of neoplasms of the liver is currently unresolved. Similar liver lesions were not seen in the mouse study, and no increase in malignant tumors of the liver and other organs was seen in either study.

Mutagenesis

Bupropion produced a positive response (2 to 3 times control mutation rate) in 2 of 5 strains in one Ames bacterial mutagenicity assay, but was negative in another. Bupropion produced an increase in chromosomal aberrations in 1 of 3 in vivo rat bone marrow cytogenetic studies.

Impairment of Fertility

A fertility study in rats at doses up to 300 mg/kg/day revealed no evidence of impaired fertility (approximately 6 times the MRHD on a mg/m^2 basis).

14 CLINICAL STUDIES

14.1 Major Depressive Disorder

The efficacy of bupropion in the treatment of major depressive disorder was established with the immediate-release formulation of bupropion hydrochloride in two 4-week, placebo-controlled trials in adult inpatients with MDD and in one 6-week, placebo-controlled trial in adult outpatients with MDD. In the first study, the bupropion dose range was 300 mg to 600 mg per day administered in 3 divided doses; 78% of patients were treated with doses of 300 mg to 450 mg per day. The trial demonstrated the efficacy of bupropion as measured by the Hamilton Depression Rating Scale (HAMD) total score, the HAMD depressed mood item (item 1), and the Clinical Global Impressions-Severity Scale (CGI-S). The second study included 2 fixed doses of bupropion (300 mg and 450 mg per day) and placebo. This trial demonstrated the efficacy of bupropion for only the 450 mg dose. The efficacy results were significant for the HAMD total score and the CGI-S severity score, but not for HAMD item 1. In the third study, outpatients were treated with bupropion 300 mg per day. This study demonstrated the efficacy of bupropion as measured by the HAMD total score, the HAMD item 1, the Montgomery-Asberg Depression Rating Scale (MADRS), the CGI-S score, and the CGI-Improvement Scale (CGI-I) score.

A longer-term, placebo-controlled, randomized withdrawal trial demonstrated the efficacy of bupropion HCl sustained-release in the maintenance treatment of MDD. The trial included adult outpatients meeting DSM-IV criteria for MDD, recurrent type, who had responded during an 8-week open-label trial of bupropion 300 mg per day. Responders were randomized to continuation of bupropion 300 mg per day or placebo for up to 44 weeks of observation for relapse. Response during the open-label phase was defined as a CGI-Improvement Scale score of 1 (very much improved) or 2 (much improved) for each of the final 3 weeks. Relapse during the double-blind phase was defined as the investigator’s judgment that drug treatment was needed for worsening depressive symptoms. Patients in the bupropion group experienced significantly lower relapse rates over the subsequent 44 weeks compared to those in the placebo group.

Although there are no independent trials demonstrating the efficacy of APLENZIN or bupropion HCl extended-release in the acute treatment of MDD, studies have demonstrated similar bioavailability between the immediate-, sustained-, and extended-release formulations of bupropion HCl under steady-state conditions (i.e., the exposures [Cmax and AUC] for bupropion and its metabolites are similar among the 3 formulations). Furthermore, clinical studies have demonstrated that APLENZIN is bioequivalent to bupropion HCl extended-release.

14.2 Seasonal Affective Disorder

The efficacy of bupropion hydrochloride extended-release in the prevention of seasonal major depressive episodes associated with SAD was established in 3 randomized, double-blind, placebo-controlled trials in adult outpatients with a history of MDD with an autumn-winter seasonal pattern (as defined by DSM-IV criteria). Bupropion treatment was initiated prior to the onset of symptoms in the autumn (September to November). Treatment was discontinued following a 2-week taper that began during the first week of spring (fourth week of March), resulting in a treatment duration of approximately 4 to 6 months for the majority of patients. Patients were randomized to treatment with bupropion HCl extended-release or placebo. The initial bupropion dose was 150 mg once daily for 1 week, followed by up-titration to 300 mg once daily. Patients who were deemed by the investigator to be unlikely or unable to tolerate 300 mg once daily were allowed to remain on, or had their dose reduced to, 150 mg once daily. The mean bupropion doses in the 3 trials ranged from 257 mg to 280 mg per day. Approximately 59% of patients continued in the study for 3 to 6 months; 26% continued for <3 months, 15% continued for >6 months.

To enter the trials, patients must have had a low level of depressive symptoms, as demonstrated by a score of <7 on the Hamilton Depression Rating Scale-17 (HAMD17) and a HAMD24 score of <14. The primary efficacy measure was the Structured Interview Guide for the Hamilton Depression Rating Scale, Seasonal Affective Disorders (SIGH-SAD), which is identical to the HAMD24. The SIGH-SAD consists of the HAMD17 plus 7 items specifically assessing core symptoms of seasonal affective disorder: social withdrawal, weight gain, increased appetite, increased eating, carbohydrate craving, hypersomnia, and fatigability. The primary efficacy endpoint was the onset of a seasonal major depressive episode. The criteria for defining an episode included: 1) the investigator’s judgment that a major depressive episode had occurred or that the patient required intervention for depressive symptoms, or 2) a SIGH-SAD score of >20 on 2 consecutive weeks. The primary analysis was a comparison of depression-free rates between the bupropion and placebo groups.

In these 3 trials, the percentage of patients who were depression-free (did not have an episode of MDD) at the end of treatment was significantly higher in the bupropion group than in the placebo group: 81.4% vs. 69.7%, 87.2% vs. 78.7%, and 84.0% vs. 69.0% for Trials 1, 2 and 3, respectively. For the 3 trials combined, the depression-free rate was 84.3% versus 72.0% in the bupropion and placebo group, respectively.

16 HOW SUPPLIED/STORAGE AND HANDLING

APLENZIN® Extended-Release Tablets, 174 mg of bupropion hydrobromide, are white to off-white, round tablets printed on one side with black ink “BR” over “174” in bottles of 30 tablets (NDC 0187-5810-30).

APLENZIN® Extended-Release Tablets, 348 mg of bupropion hydrobromide, are white to off-white, round tablets printed on one side with black ink “BR” over “348” in bottles of 30 tablets (NDC 0187-5811-30).

APLENZIN® Extended-Release Tablets, 522 mg of bupropion hydrobromide, are white to off-white, round tablets printed on one side with black ink “BR” over “522” in bottles of 30 tablets (NDC 0187-5812-30).

STORAGE AND HANDLING

Store at 25°C (77°F); excursions permitted to 15° to 30°C (59° to 86°F) [see USP Controlled Room Temperature].

17 PATIENT COUNSELING INFORMATION

Advise the patient to read the FDA-approved patient labeling (Medication Guide).

Suicidal Thoughts and Behaviors

Instruct patients, their families, and/or their caregivers to be alert to the emergence of anxiety, agitation, panic attacks, insomnia, irritability, hostility, aggressiveness, impulsivity, akathisia (psychomotor restlessness), hypomania, mania, other unusual changes in behavior, worsening of depression, and suicidal ideation, especially early during antidepressant treatment and when the dose is adjusted up or down. Advise families and caregivers of patients to observe for the emergence of such symptoms on a day-to-day basis, since changes may be abrupt. Such symptoms should be reported to the patient’s prescriber or health professional, especially if they are severe, abrupt in onset, or were not part of the patient’s presenting symptoms. Symptoms such as these may be associated with an increased risk for suicidal thinking and behavior and indicate a need for very close monitoring and possibly changes in the medication.

Neuropsychiatric Adverse Events and Suicide Risk in Smoking Cessation Treatment

Although APLENZIN is not indicated for smoking cessation treatment, it contains the same active ingredient as ZYBAN which is approved for this use. Inform patients that some patients have experienced changes in mood (including depression and mania), psychosis, hallucinations, paranoia, delusions, homicidal ideation, aggression, hostility, agitation, anxiety, and panic, as well as suicidal ideation and suicide when attempting to quit smoking while taking bupropion. Instruct patients to discontinue APLENZIN and contact a healthcare professional if they experience such symptoms [see Warnings and Precautions (5.2) and Adverse Reactions (6.2)].

Severe Allergic Reactions

Educate patients on the symptoms of hypersensitivity and to discontinue APLENZIN if they have a severe allergic reaction.

Seizure

Instruct patients to discontinue and not restart APLENZIN if they experience a seizure while on treatment. Advise patients that the excessive use or the abrupt discontinuation of alcohol, benzodiazepines, antiepileptic drugs, or sedatives/hypnotics can increase the risk of seizure. Advise patients to minimize or avoid the use of alcohol.

Angle-Closure Glaucoma

Patients should be advised that taking APLENZIN can cause mild pupillary dilation, which in susceptible individuals, can lead to an episode of angle-closure glaucoma. Pre-existing glaucoma is almost always open-angle glaucoma because angle-closure glaucoma, when diagnosed, can be treated definitively with iridectomy. Open-angle glaucoma is not a risk factor for angle-closure glaucoma. Patients may wish to be examined to determine whether they are susceptible to angle closure, and have a prophylactic procedure (e.g., iridectomy), if they are susceptible [see Warnings and Precautions (5.7)].

Bupropion-Containing Products

Educate patients that APLENZIN contains the same active ingredient (bupropion) found in ZYBAN, which is used as an aid to smoking cessation treatment, and that APLENZIN should not be used in combination with ZYBAN or any other medications that contain bupropion hydrochloride (such as WELLBUTRIN XL, the extended-release formulation, WELLBUTRIN SR, the sustained-release formulation, and WELLBUTRIN, the immediate-release formulation). In addition, there are a number of generic bupropion HCl products for the immediate, sustained, and extended-release formulations.

Potential for Cognitive and Motor Impairment

Advise patients that any CNS-active drug like APLENZIN tablets may impair their ability to perform tasks requiring judgment or motor and cognitive skills. Advise patients that until they are reasonably certain that APLENZIN tablets do not adversely affect their performance, they should refrain from driving an automobile or operating complex, hazardous machinery. APLENZIN treatment may lead to decreased alcohol tolerance.

Concomitant Medications

Counsel patients to notify their healthcare provider if they are taking or plan to take any prescription or over-the-counter drugs, because APLENZIN tablets and other drugs may affect each other’s metabolism.

Pregnancy

Advise patients to notify their healthcare provider if they become pregnant or intend to become pregnant during therapy with APLENZIN. Advise patients that there is a pregnancy exposure registry that monitors pregnancy outcomes in women exposed to APLENZIN during pregnancy [see Use in Specific Populations (8.1)].

Administration Information

Instruct patients to swallow APLENZIN tablets whole so that the release rate is not altered. Instruct patients if they miss a dose, not to take an extra tablet to make up for the missed dose and to take the next tablet at the regular time because of the dose-related risk of seizure. Instruct patients that APLENZIN tablets should be swallowed whole and not crushed, divided, or chewed. APLENZIN can be taken with or without food.

Distributed by:
Bausch Health US, LLC
Bridgewater, NJ 08807 USA

Manufactured by:
Bausch Health Companies Inc.
Steinbach, MB R5G 1Z7, Canada

APLENZIN is a registered trademark of Bausch Health Companies Inc. or its affiliates.

Wellbutrin XL is a registered trademark of GlaxoSmithKline LLC used under license.

All other product/brand names and/or logos are the trademarks of their respective owners.

U.S. Patent Numbers: 7,241,805; 7,569,610; 7,572,935; 7,585,897; 7,645,802; 7,649,019; 7,662,407 and 7,671,094

© 2025 Bausch Health Companies Inc. or its affiliates

9386812 20006032

MEDICATION GUIDE

APLENZIN® (uh-PLEN-zin)

(bupropion hydrobromide) extended-release tablets

IMPORTANT: Be sure to read the three sections of this Medication Guide. The first section is about the risk of suicidal thoughts and actions with antidepressant medicines; the second section is about the risk of changes in thinking and behavior, depression and suicidal thoughts or actions with medicines used to quit smoking; and the third section is entitled “What Other Important Information Should I Know About APLENZIN?”

Antidepressant Medicines, Depression and Other Serious

Mental Illnesses, and Suicidal Thoughts or Actions

This section of the Medication Guide is only about the risk of suicidal thoughts and actions with antidepressant medicines.

What is the most important information I should know about antidepressant medicines, depression and other serious mental illnesses, and suicidal thoughts or actions?

1. Antidepressant medicines may increase the risk of suicidal thoughts or actions in some children, teenagers, or young adults within the first few months of treatment.
2. Depression or other serious mental illnesses are the most important causes of suicidal thoughts and actions. Some people may have a particularly high risk of having suicidal thoughts or actions. These include people who have (or have a family history of) bipolar illness (also called manic-depressive illness) or suicidal thoughts or actions.
3. How can I watch for and try to prevent suicidal thoughts and actions in myself or a family member?
4. Pay close attention to any changes, especially sudden changes, in mood, behaviors, thoughts, or feelings. This is very important when an antidepressant medicine is started or when the dose is changed.
5. Call your healthcare provider right away to report new or sudden changes in mood, behavior, thoughts, or feelings.
6. Keep all follow-up visits with your healthcare provider as scheduled. Call the healthcare provider between visits as needed, especially if you have concerns about symptoms.

Call your healthcare provider right away if you or your family member has any of the following symptoms, especially if they are new, worse, or worry you:

- thoughts about suicide or dying
- attempts to commit suicide
- new or worse depression
- new or worse anxiety
- feeling very agitated or restless
- panic attacks
- trouble sleeping (insomnia)
- new or worse irritability
- acting aggressive, being angry, or violent
- acting on dangerous impulses
- an extreme increase in activity and talking (mania)
- other unusual changes in behavior or mood

What else do I need to know about antidepressant medicines?

- Never stop an antidepressant medicine without first talking to a healthcare provider. Stopping an antidepressant medicine suddenly can cause other symptoms.
- Antidepressants are medicines used to treat depression and other illnesses. It is important to discuss all the risks of treating depression and also the risks of not treating it. Patients and their families or other caregivers should discuss all treatment choices with the healthcare provider, not just the use of antidepressants.
- Antidepressant medicines have other side effects. Talk to the healthcare provider about the side effects of the medicine prescribed for you or your family member.
- Antidepressant medicines can interact with other medicines. Know all of the medicines that you or your family member takes. Keep a list of all medicines to show the healthcare provider. Do not start new medicines without first checking with your healthcare provider.

It is not known if APLENZIN is safe and effective in children under the age of 18.

Quitting Smoking, Quit-Smoking Medications, Changes in Thinking and Behavior, Depression, and Suicidal Thoughts or Actions

This section of the Medication Guide is only about the risk of changes in thinking and behavior, depression and suicidal thoughts or actions with drugs used to quit smoking. Although APLENZIN is not a treatment for quitting smoking, it contains the same active ingredient (bupropion) as ZYBAN which is used to help patients quit smoking.

Talk to your healthcare provider or your family member’s healthcare provider about:

- all risks and benefits of quit-smoking medicines.
- all treatment choices for quitting smoking.

When you try to quit smoking, with or without bupropion you may have symptoms that may be due to nicotine withdrawal, including:

- urge to smoke
- trouble sleeping
- frustration
- feeling anxious
- restlessness
- increased appetite

- depressed mood
- irritability
- anger
- difficulty concentrating
- decreased heart rate
- weight gain

Some people have even experienced suicidal thoughts when trying to quit smoking without medication. Sometimes quitting smoking can lead to worsening of mental health problems that you already have, such as depression.

Some people have had serious side effects while taking bupropion to help them quit smoking, including: New or worse mental health problems, such as changes in behavior or thinking, aggression, hostility, agitation, depression, or suicidal thoughts or actions. Some people had these symptoms when they began taking bupropion, and others developed them after several weeks of treatment, or after stopping bupropion. These symptoms happened more often in people who had a history of mental health problems before taking bupropion than in people without a history of mental health problems.

Stop taking APLENZIN and call your healthcare provider right away if you, your family, or caregiver notice any of these symptoms. Work with your healthcare provider to decide whether you should continue to take APLENZIN. In many people, these symptoms went away after stopping APLENZIN, but in some people symptoms continued after stopping APLENZIN. It is important for you to follow up with your healthcare provider until your symptoms go away. Before taking APLENZIN, tell your healthcare provider if you have ever had depression or other mental health problems. You should also tell your healthcare provider about any symptoms you had during other times you tried to quit smoking, with or without bupropion.

What Other Important Information Should I Know About APLENZIN?

- Seizures: There is a chance of having a seizure (convulsion, fit) with APLENZIN, especially in people:
- with certain medical problems
- who take certain medicines.

The chance of having seizures increases with higher doses of APLENZIN. For more information, see the sections “Who should not take APLENZIN?” and “What should I tell my healthcare provider before taking APLENZIN?” Tell your healthcare provider about all of your medical conditions and all the medicines you take.

Do not take any other medicines while you are taking APLENZIN unless your healthcare provider has said it is okay to take them.

If you have a seizure while taking APLENZIN, stop taking the tablets and call your healthcare provider right away. Do not take APLENZIN again if you have a seizure.

- High blood pressure (hypertension). Some people get high blood pressure that can be severe, while taking APLENZIN. The chance of high blood pressure may be higher if you also use nicotine replacement therapy (such as a nicotine patch) to help you stop smoking (see the section of this Medication Guide called “How should I take APLENZIN?”).
- Manic episodes. Some people may have periods of mania while taking APLENZIN, including:
- Greatly increased energy
- Severe trouble sleeping
- Racing thoughts
- Reckless behavior
- Unusually grand ideas
- Excessive happiness or irritability
- Talking more or faster than usual

If you have any of the above symptoms of mania, call your healthcare provider.

- Unusual thoughts or behaviors. Some patients have unusual thoughts or behaviors while taking APLENZIN, including delusions (believe you are someone else), hallucinations (seeing or hearing things that are not there), paranoia (feeling that people are against you), or feeling confused. If this happens to you, call your healthcare provider.
- Visual problems.
- eye pain
- changes in vision
- swelling or redness in or around the eye

Only some people are at risk for these problems. You may want to undergo an eye examination to see if you are at risk and receive preventative treatment if you are.

- Severe allergic reactions. Some people can have severe allergic reactions to APLENZIN. Stop taking APLENZIN and call your healthcare provider right away if you get a rash, itching, hives, fever, swollen lymph glands, painful sores in the mouth or around the eyes, swelling of the lips or tongue, chest pain, or have trouble breathing. These could be signs of a serious allergic reaction.

What is APLENZIN?

APLENZIN is a prescription medicine used to treat adults with a certain type of depression called major depressive disorder and for the prevention of autumn-winter seasonal depression (seasonal affective disorder).

Who should not take APLENZIN?

Do not take APLENZIN if you:

- have or had a seizure disorder or epilepsy.
- have or had an eating disorder such as anorexia nervosa or bulimia.
- are taking any other medicines that contain bupropion, including WELLBUTRIN, WELLBUTRIN SR, WELLBUTRIN XL, ZYBAN, or FORFIVO XL. Bupropion is the same active ingredient that is in APLENZIN.
- drink a lot of alcohol and abruptly stop drinking, or take medicines called sedatives (these make you sleepy), benzodiazepines, or anti-seizure medicines, and you stop taking them all of a sudden.
- take a monoamine oxidase inhibitor (MAOI). Ask your healthcare provider or pharmacist if you are not sure if you take an MAOI, including the antibiotic linezolid.
- do not take an MAOI within 2 weeks of stopping APLENZIN unless directed to do so by your healthcare provider.
- do not start APLENZIN if you stopped taking an MAOI in the last 2 weeks unless directed to do so by your healthcare provider.
- are allergic to the active ingredient in APLENZIN, bupropion, or to any of the inactive ingredients. See the end of this Medication Guide for a complete list of ingredients in APLENZIN.

What should I tell my healthcare provider before taking APLENZIN?

Tell your healthcare provider if you have ever had depression, suicidal thoughts or actions, or other mental health problems. You should also tell your healthcare provider about any symptoms you had during other times you tried to quit smoking, with or without APLENZIN. See “Quitting Smoking, Quit-Smoking Medications, Changes in Thinking and Behavior, Depression, and Suicidal Thoughts or Actions.”

- Tell your healthcare provider about your other medical conditions, including if you:
- have liver problems, especially cirrhosis of the liver.
- have kidney problems.
- have, or have had, an eating disorder such as anorexia nervosa or bulimia.
- have had a head injury.
- have had a seizure (convulsion, fit).
- have a tumor in your nervous system (brain or spine).
- have had a heart attack, heart problems, or high blood pressure.
- are a diabetic taking insulin or other medicines to control your blood sugar.
- drink alcohol.
- abuse prescription medicines or street drugs.
- are pregnant or plan to become pregnant.
- Talk to your healthcare provider about the risk to your unborn baby if you take APLENZIN during pregnancy.
- Tell your healthcare provider if you become pregnant or think you are pregnant during treatment with APLENZIN.
If you become pregnant during treatment with APLENZIN, talk to your healthcare provider about registering with the National Pregnancy Registry for Antidepressants. You can register by calling 1-844-405-6185.
- are breastfeeding or plan to breastfeed during treatment with APLENZIN. APLENZIN passes into your milk. Talk to your healthcare provider about the best way to feed your baby during treatment with APLENZIN.

Tell your healthcare provider about all the medicines you take, including prescription, over-the-counter medicines, vitamins, and herbal supplements. Many medicines increase your chances of having seizures or other serious side effects if you take them while you are taking APLENZIN.

How should I take APLENZIN?

- Take APLENZIN exactly as prescribed by your healthcare provider. Do not change your dose or stop taking APLENZIN without talking with your healthcare provider first.
- Swallow APLENZIN tablets whole. Do not chew, cut, or crush APLENZIN tablets. If you do, the medicine will be released into your body too quickly. If this happens you may be more likely to get side effects including seizures. Tell your healthcare provider if you cannot swallow tablets.
- APLENZIN tablets may have an odor. This is normal.
- Take your doses of APLENZIN at least 24 hours apart.
- You may take APLENZIN with or without food.
- If you miss a dose, do not take an extra dose to make up for the dose you missed. Wait and take your next dose at the regular time. This is very important. Too much APLENZIN can increase your chance of having a seizure.
- If you take too much APLENZIN, or overdose, call your local emergency room or poison control center right away.
- Do not take any other medicines while taking APLENZIN unless your healthcare provider has told you it is okay.
- If you are taking APLENZIN for the treatment of major depressive disorder, it may take several weeks for you to feel that APLENZIN is working. Once you feel better, it is important to keep taking APLENZIN exactly as directed by your healthcare provider. Call your healthcare provider if you do not feel APLENZIN is working for you.

What should I avoid while taking APLENZIN?

- Limit or avoid using alcohol during treatment with APLENZIN. If you usually drink a lot of alcohol, talk with your healthcare provider before suddenly stopping. If you suddenly stop drinking alcohol, you may increase your chance of having seizures.
- Do not drive a car or use heavy machinery until you know how APLENZIN affects you. APLENZIN can affect your ability to do these things safely.

What are possible side effects of APLENZIN?

APLENZIN can cause serious side effects. See the sections at the beginning of this Medication Guide for information about serious side effects of APLENZIN.

The most common side effects of APLENZIN include:

- trouble sleeping
- stuffy nose
- dry mouth
- dizziness

- feeling anxious
- nausea
- constipation
- joint aches

If you have trouble sleeping, do not take APLENZIN too close to bedtime.

Tell your healthcare provider right away about any side effects that bother you.

These are not all the possible side effects of APLENZIN. For more information, ask your healthcare provider or pharmacist.

Call your doctor for medical advice about side effects. You may report side effects to FDA at 1-800-FDA-1088.

You may also report side effects to Bausch Health US, LLC at 1-800-321-4576.

How should I store APLENZIN?

- Store APLENZIN at 77°F (25°C).

Keep APLENZIN and all medicines out of the reach of children.

General information about the safe and effective use of APLENZIN.

Medicines are sometimes prescribed for purposes other than those listed in a Medication Guide. Do not use APLENZIN for a condition for which it was not prescribed. Do not give APLENZIN to other people, even if they have the same symptoms you have. It may harm them.

If you take a urine drug screening test, APLENZIN may make the test result positive for amphetamines. If you tell the person giving you the drug screening test that you are taking APLENZIN, they can do a more specific drug screening test that should not have this problem.

This Medication Guide summarizes important information about APLENZIN. If you would like more information, talk with your healthcare provider. You can ask your healthcare provider or pharmacist for information about APLENZIN that is written for health professionals.

For more information about APLENZIN, go to www.APLENZIN.com or call 1-800-321-4576.

What are the ingredients in APLENZIN?

Active ingredient: bupropion hydrobromide

Inactive ingredients: ethylcellulose, glyceryl dibehenate, polyvinyl alcohol, polyethylene glycol, povidone, and dibutyl sebacate. Carnauba wax is included in the 174 mg and 348 mg strengths. The tablets are printed with edible black ink.

Distributed by:

Bausch Health US, LLC

Bridgewater, NJ 08807 USA

Manufactured by:

Bausch Health Companies Inc.

Steinbach, MB R5G 1Z7, Canada

APLENZIN is a registered trademark of Bausch Health Companies Inc. or its affiliates.

Wellbutrin XL is a registered trademark of GlaxoSmithKline LLC used under license.

All other product/brand names and/or logos are the trademarks of their respective owners.

U.S. Patent Numbers: 7,241,805; 7,569,610; 7,572,935; 7,585,897; 7,645,802; 7,649,019; 7,662,407 and 7,671,094

© 2025 Bausch Health Companies Inc. or its affiliates

This Medication Guide has been approved by the U.S. Food and Drug Administration.
Revised: 11/2025

9386812 20006032

PRINCIPAL DISPLAY PANEL - 174 mg Tablet Bottle Label

NDC 0187-5810-30
ONCE DAILY
Aplenzin®
(bupropion hydrobromide)
Extended-Release Tablets

174 mg

WARNING: Do not use with other
medicines that contain bupropion.

Federal Law requires dispensing of
Aplenzin with the Medication Guide
attached to this bottle.

Rx only

30 Tablets

BAUSCH Health

9422105

PRINCIPAL DISPLAY PANEL - 348 mg Tablet Bottle Label

NDC 0187-5811-30
ONCE DAILY
Aplenzin®
(bupropion hydrobromide)
Extended-Release Tablets

348 mg

WARNING: Do not use with other
medicines that contain bupropion.

Federal Law requires dispensing of
Aplenzin with the Medication Guide
attached to this bottle.

Rx only

30 Tablets

BAUSCH Health

9422305

PRINCIPAL DISPLAY PANEL - 522 mg Tablet Bottle Label

NDC 0187-5812-30
ONCE DAILY
Aplenzin®
(bupropion hydrobromide)
Extended-Release Tablets

522 mg

WARNING: Do not use with other
medicines that contain bupropion.

Federal Law requires dispensing of
Aplenzin with the Medication Guide
attached to this bottle.

30 Tablets

Rx only

BAUSCH Health

9422505